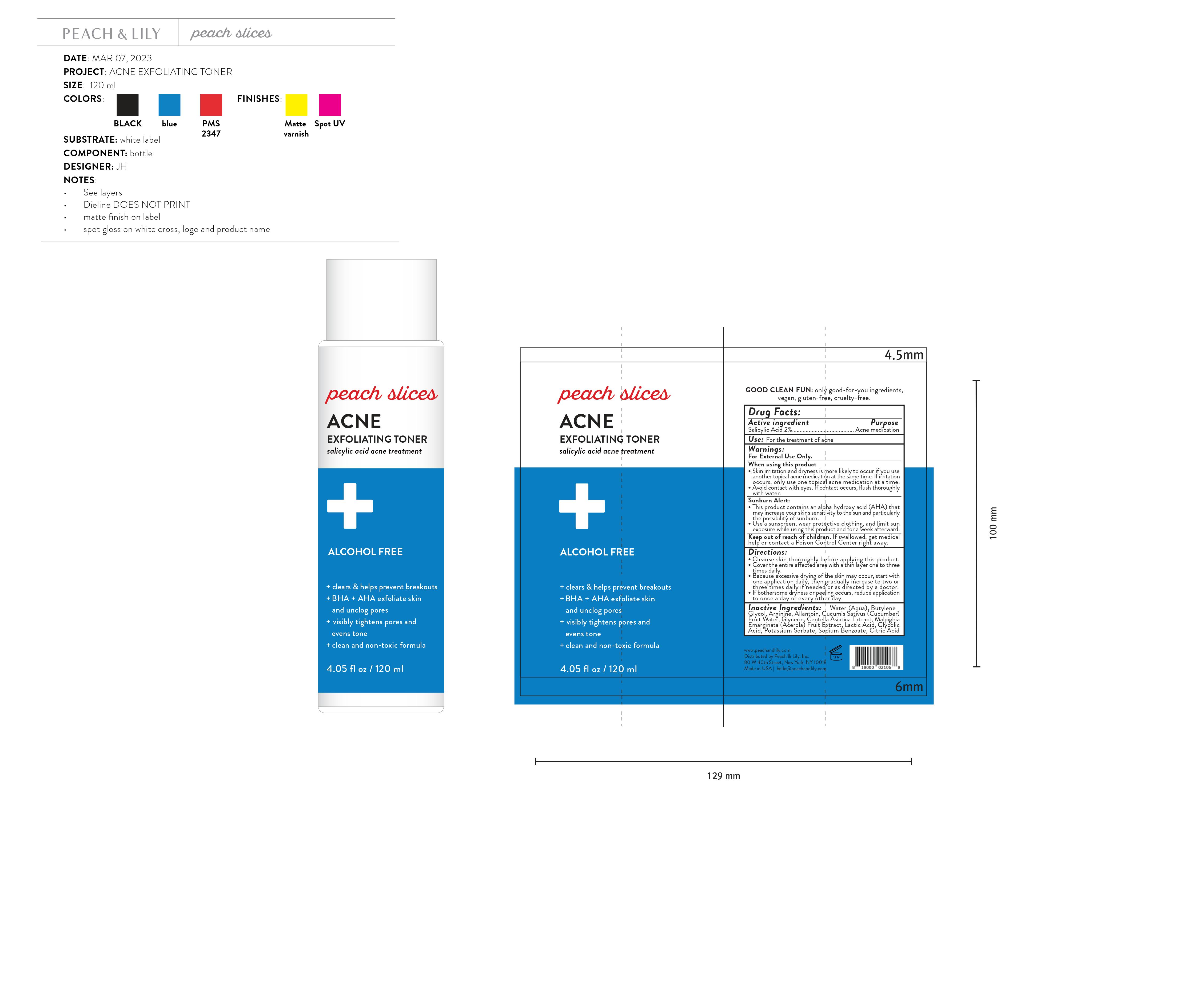 DRUG LABEL: Peach and Lily Peaches Slices Acne Exfoliating toner
NDC: 81515-501 | Form: LIQUID
Manufacturer: Peach & Lily Inc.
Category: otc | Type: HUMAN OTC DRUG LABEL
Date: 20231028

ACTIVE INGREDIENTS: SALICYLIC ACID 20 mg/1 mL
INACTIVE INGREDIENTS: WATER; BUTYLENE GLYCOL; ARGININE; ALLANTOIN; CUCUMBER FRUIT OIL; GLYCERIN; CENTELLA ASIATICA WHOLE; ACEROLA; LACTIC ACID; GLYCOLIC ACID; POTASSIUM SORBATE; SODIUM BENZOATE; CITRIC ACID MONOHYDRATE

Peach & Lily Peaches Slices Acne Exfoliating toner

Active ingredient

Salicylic Acid 2%

Purpose

Acne medication

Use:

For the treatment of acne

Warnings:

For External use only.

When using this product

- Skin irritation and dryness is more likely to occur if you use another topical acne medication at the same time. If irritation occurs, only use one topical acne medication at a time.
- Avoid contact with eyes. If contact occurs, flush thoroughly with water.

- This product contains an alpha hydroxy acid (AHA) that may increase your skin's sensitivity to the sun and particularly the possibility of sunburn.
- Use a sunscreen, wear protective clothing, and limit sun exposure while using this product and for a week afterward.

Sunburn Alert:

Keep out of reach of children.

If swallowed, get medical help or contact a Poison Control Center right away.

Directions:

- Cleanse skin thoroughly before applying this product.
- Cover the entire affected area with a thin layer one to three times daily.
- Because excessive drying of the skin may occur, start with one application daily, then gradually increase to two or three times daily if needed or as directed by a doctor.
- If bothersome dryness or peeling occurs, reduce application to once a day or every other day.

Inactive Ingredients:

Water (Aqua), Butylene Glycol, Arginine, Allantoin, Cucumis Sativus (Cucumber) Fruit Water, Glycerin, Centella Asiatica Extract, Malpighia Emarginata (Acerola) Fruit Extract, Lactic Acid, Glycolic Acid, Potassium Sorbate, Sodium Benzoate, Citric Acid